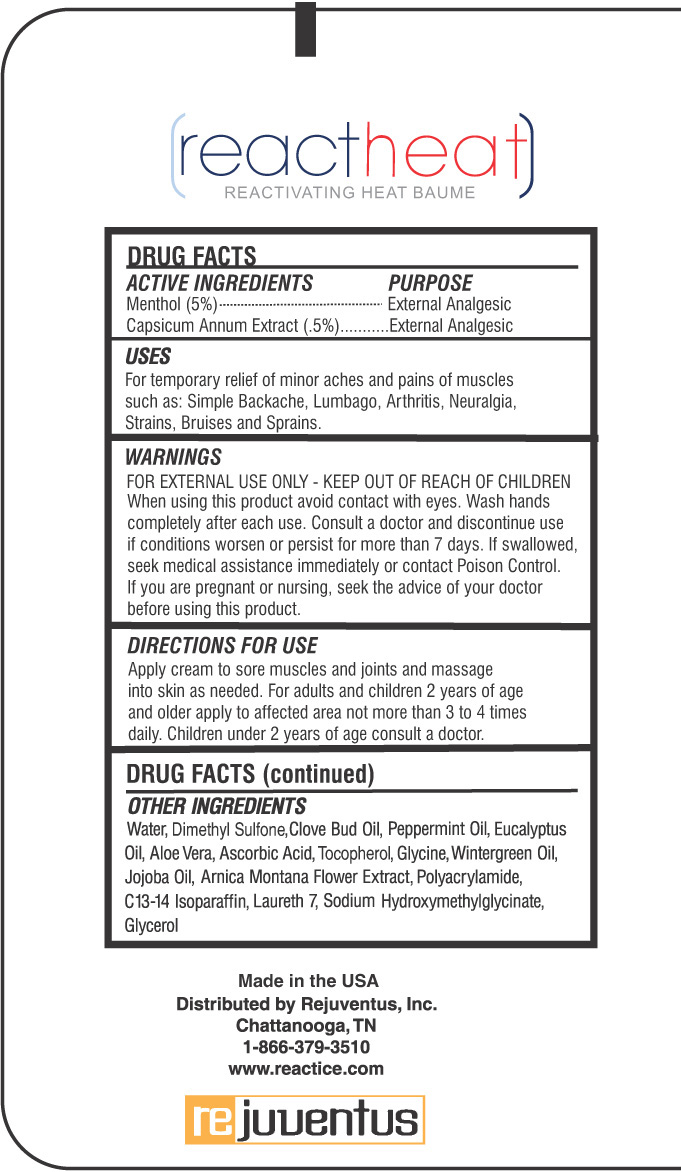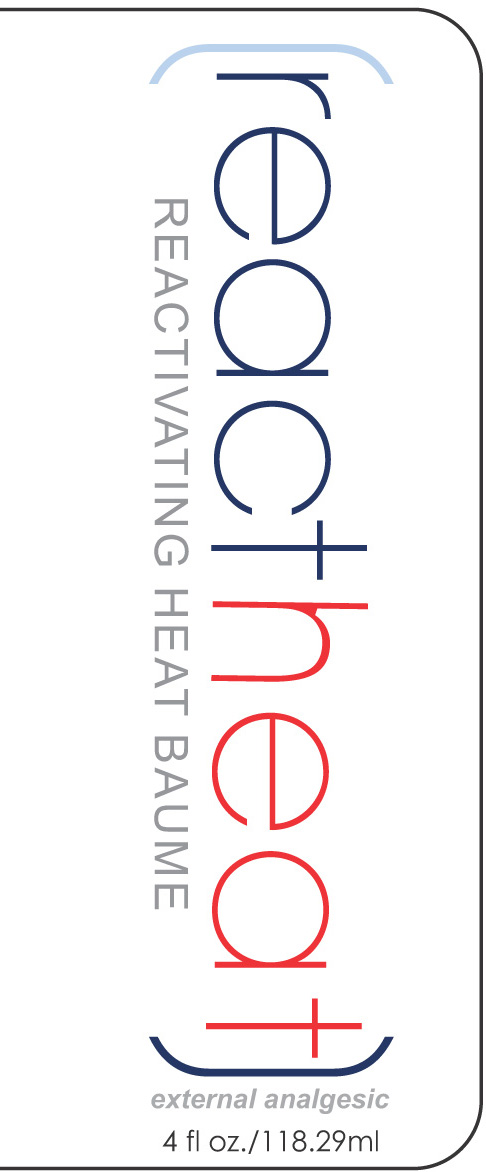 DRUG LABEL: Reactheat
NDC: 75963-126 | Form: CREAM
Manufacturer: Rejuventus
Category: otc | Type: HUMAN OTC DRUG LABEL
Date: 20120127

ACTIVE INGREDIENTS: MENTHOL 5 mL/100 mL; BIRD PEPPER 0.5 mL/100 mL
INACTIVE INGREDIENTS: WATER; DIMETHYL SULFONE; CLOVE OIL; PEPPERMINT OIL; EUCALYPTUS OIL; ALOE VERA LEAF; ASCORBIC ACID; TOCOPHEROL; GLYCINE; JOJOBA OIL; ARNICA MONTANA FLOWER; C13-14 ISOPARAFFIN; LAURETH-7; SODIUM HYDROXYMETHYLGLYCINATE; GLYCERIN

Reactheat Reactivating Heat Baume

Active Ingredients Purpose

Menthol (5%) External Analgesic

Capsicum Annum Extract (0.5) External Analgesic

Uses

For temporary relief of minor aches and pains of muscles such as: simple backache, lumbago, arthritis, neuralgia, strains, bruises and sprains.

Keep out of reach of children

INDICATIONS AND USAGE

Consult a doctor and discontinue use if condition worsens or persists for more than 7 days.

WARNINGS

For external use only. When using this product, avoid contact with eyes. Wash hands completely after each use. If swallowed seek medical assistance immediately or contact poison control. If you are pregnant or nursing, seeking the advice of your doctor before using this product.

DOSAGE AND ADMINISTRATION

Directions for use

Apply cream to sore muscles and joints and massage into skin as needed. For adults and children 2 years of age and older apply to affected area no more than 3 to 4 times daily. Children under 2 years of age consult a doctor.

INACTIVE INGREDIENT

Water, DImethyl Sulfone, Clove Bud Oil, Peppermint Oil, Eucalyptus Oil, Aloe vera, Ascorbic Acid, Tocopherol, Glycine, Wintergreen Oil, Jojoba Oil, Arnica Montana Flower Extract, Polyarylamide, C13-14 Isoparaffin, Laureth 7, Sodium Hydroxymethylglycinate, glycerol.

PACKAGE LABEL

Reactheat
Reactivating Heat Baume
4 fl. oz./ 118.29ml